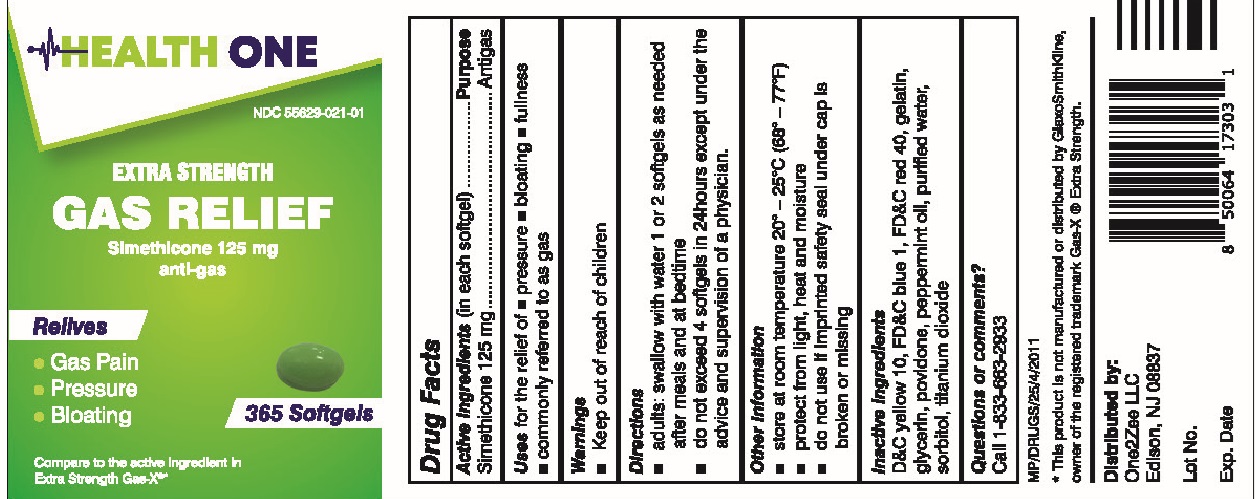 DRUG LABEL: Simethicone 125MG Gas Relief
NDC: 55629-021 | Form: CAPSULE, LIQUID FILLED
Manufacturer: One2Zee Limited Liability Company
Category: otc | Type: HUMAN OTC DRUG LABEL
Date: 20240925

ACTIVE INGREDIENTS: DIMETHICONE 125 mg/1 1
INACTIVE INGREDIENTS: D&C YELLOW NO. 10; FD&C BLUE NO. 1; FD&C RED NO. 40; GELATIN; GLYCERIN; POVIDONE; PEPPERMINT OIL; WATER; SORBITOL; TITANIUM DIOXIDE

Simethicone 125mg Gas Relief

Active Ingredients (in each softgel)

Simethicone 125 mg

Purpose

Antigas

INDICATIONS AND USAGE

Use for the relief of

- pressure
- bloating
- fullness
- commonly referred to as gas

Directions

- adults:swallow with water 1 or 2 softgels as needed after meals and at bedtime
- do not exceed 4 softgels in 24 hours except under the advice and supervision of a physician

Other Information

- store at controlled room temperature 20°-25°C (68°-77°F)
- protact from light, heat and moisture
- do not use if imprinted safety seal under cap is broken or missing

INACTIVE INGREDIENT

D&C yellow 10, FD&C blue 1, FD&C red 40, gelatin, glycerin, povidone, peppermint oil, purified water, sorbitol, titanium dioxide

Questions or comments?
Call 1-833-663-2933